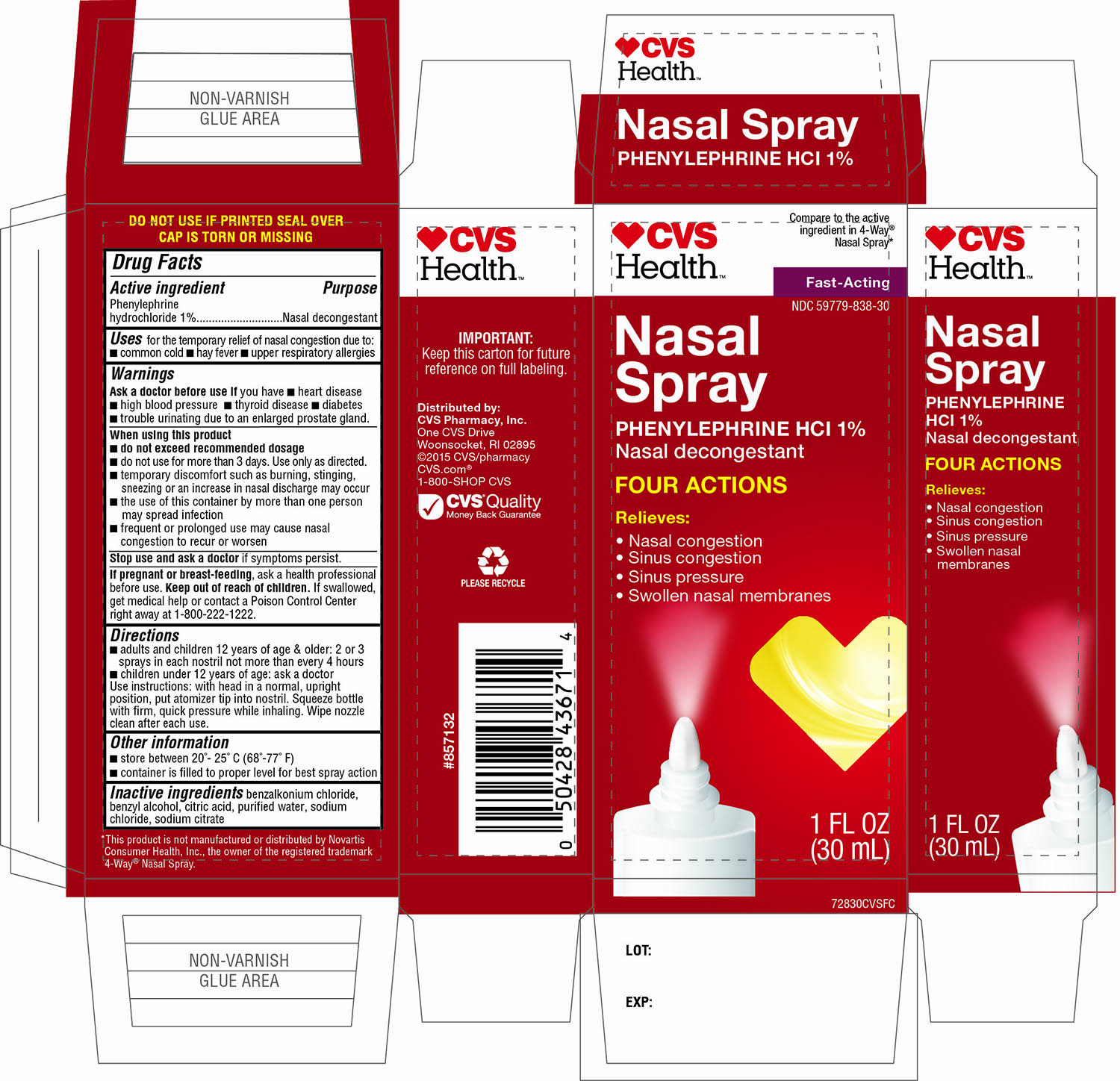 DRUG LABEL: CVS Health Four Actions Nasal Decongestant
NDC: 59779-838 | Form: SPRAY
Manufacturer: CVS Pharmacy,Inc.
Category: otc | Type: HUMAN OTC DRUG LABEL
Date: 20160922

ACTIVE INGREDIENTS: PHENYLEPHRINE HYDROCHLORIDE 10 mg/1 mL
INACTIVE INGREDIENTS: BENZALKONIUM CHLORIDE; BENZYL ALCOHOL; ANHYDROUS CITRIC ACID; WATER; SODIUM CHLORIDE; SODIUM CITRATE

CVS Health Nasal Spray Four Actions 1 FL OZ

Active ingredient

Phenylephrine hydrochloride 1%

Purpose

Nasal decongestant

Uses

for the temporary relief of nasal congestion due to:

- common cold
- hay fever
- upper respiratory allergies

Ask a doctor before use if you have

- heart disease
- high blood pressure
- thyroid disease
- diabetes
- trouble urinating due to an enlarged prostate gland.

When using this product

• do not exceed recommended dosage

• do not use more than 3 days. Use only as directed.

• temporary discomfort such as burning, stinging, sneezing, or an increase in nasal discharge may occur

• the use of this container by more than one person may spread infection

• frequent or prolonged use may cause nasal congestion to recur or worsen

Stop use and ask a doctor

if symptoms persist.

If pregnant or breast-feeding

ask a health professional before use.

Keep out of reach of children

If swallowed, get medical help or contact a Poison Control Center right away at 1-800-222-1222

Directions

- adults and children 12 years of age and older: 2 or 3 sprays in each nostril not more than every 4 hours
- children under 12 years of age: ask a doctor
- Use instructions: with head in a normal, upright position, put atomizer tip into nostril. Squeeze bottle with firm, quick pressure while inhaling. Wipe nozzle clean after each use.

Other information

- store between 20°-25°C (68°-77°F)
- container is filled to proper level for best spray action

Inactive ingredients

benzalkonium chloride, benzyl alcohol, citric acid, purified water, sodium chloride, sodium citrate

Principal Display

CVS Health ™

NDC 59779-838-30

Compare to the active ingredient 4-Way® Nasal Spray*

Fast-Acting

Nasal Spray

PHENYLEPHRINE HCl 1%

Nasal decongestant

FOUR ACTIONS

Relieves:

- Nasal congestion
- Sinus congestion
- Sinus pressure
- Swollen nasal membranes

1 FL OZ (30 mL)

DO NOT USE IF PRINTED SEAL OVER CAP IS TORN OR MISSING

*This product is not manufactured or distributed by Novartis Consumer Health, Inc., the owner of the registered trademark 4-Way® Nasal Spray.

IMPORTANT: Keep this carton for future reference on full labeling.

Distributed by:

CVS Pharmacy, Inc.

One CVS Drive

Woonsocket, RI 02895

© 2015CVS/pharmacy

CVS.com®

1-800-SHOP CVS

CVS® Quality

Money back Guarantee